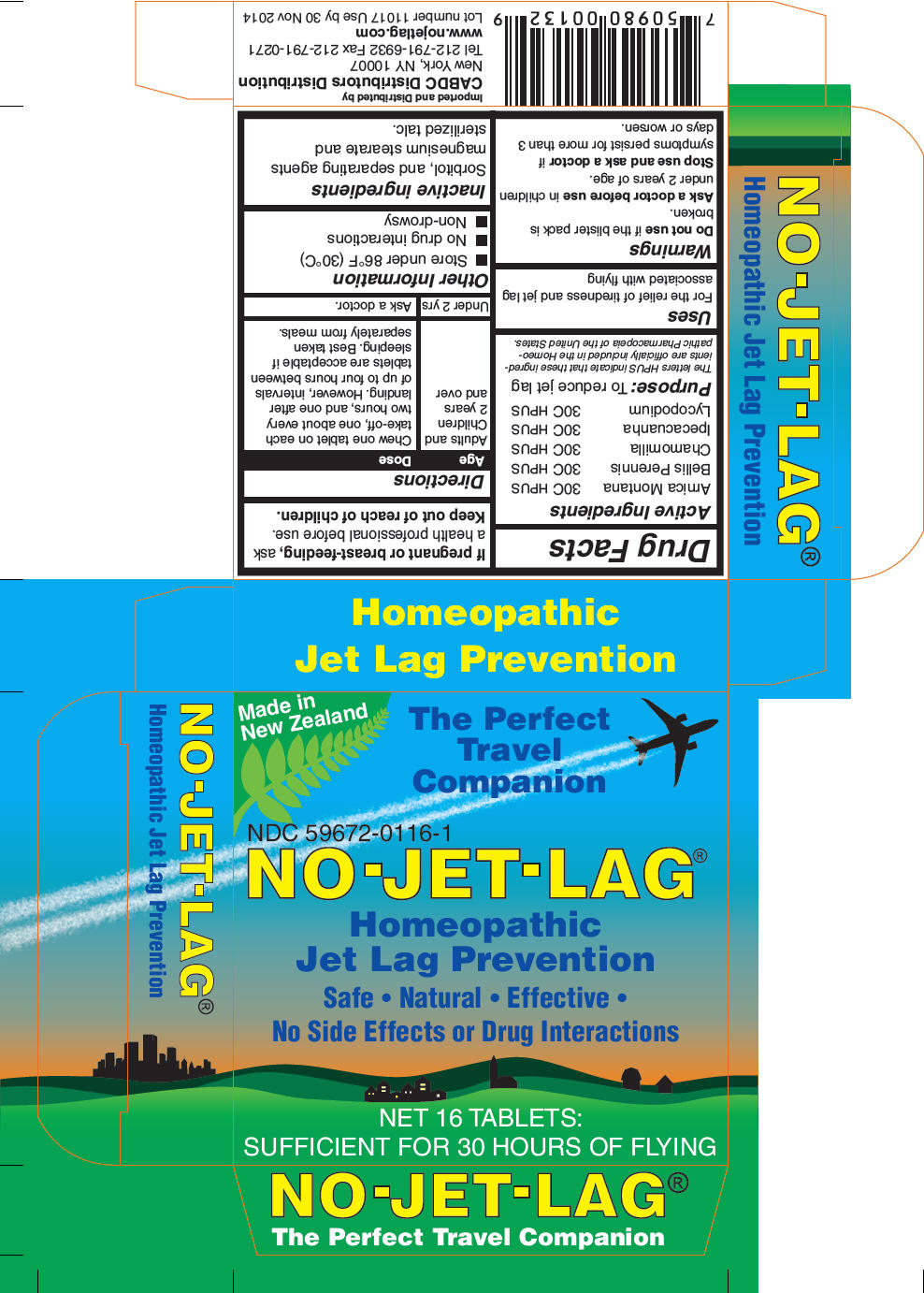 DRUG LABEL: NO-JET-LAG 
NDC: 59672-0116 | Form: TABLET
Manufacturer: Miers Laboratories
Category: homeopathic | Type: HUMAN OTC DRUG LABEL
Date: 20110815

ACTIVE INGREDIENTS: Arnica Montana 30 [hp_C]/1 1; Bellis Perennis 30 [hp_C]/1 1; Matricaria Recutita 30 [hp_C]/1 1; Ipecac 30 [hp_C]/1 1; Lycopodium Clavatum Spore 30 [hp_C]/1 1
INACTIVE INGREDIENTS: Sorbitol 242 mg/1 1; Talc; Magnesium stearate

NO-JET-LAG®
Homeopathic
Jet Lag Prevention

Drug Facts

Active Ingredients

Arnica Montana | 30C HPUS
Bellis Perennis | 30C HPUS
Chamomilla | 30C HPUS
Ipecacuanha | 30C HPUS
Lycopodium | 30C HPUS

Purpose

To reduce jet lag

The letters HPUS indicate that these ingredients are officially included in the Homeopathic Pharmacopeia of the United States.

Uses

For the relief of tiredness and jet lag associated with flying

Warnings

Do not use if the blister pack is broken.

Ask a doctor before use in children under 2 years of age.

Stop use and ask a doctor if symptoms persist for more than 3 days or worsen.

PREGNANCY OR BREAST FEEDING

If pregnant or breast-feeding, ask a health professional before use.

Keep out of reach of children.

Directions

Age | Dose
Adults and Children 2 years and over | Chew one tablet on each take-off, one about every two hours, and one after landing. However, intervals of up to four hours between tablets are acceptable if sleeping. Best taken separately from meals.
Under 2 yrs | Ask a doctor.

Other Information

- Store under 86°F (30°C)
- No drug interactions
- Non-drowsy

Inactive ingredients

Sorbitol, and separating agents magnesium stearate and sterilized talc.

Imported and Distributed by
CABDC Distributors Distribution
New York, NY 10007
Tel 212-791-6932 Fax 212-791-0271

PRINCIPAL DISPLAY PANEL - 16 Tablet Carton

Made in
New Zealand

The Perfect
Travel
Companion

NDC 59672-0116-1

NO-JET-LAG®

Homeopathic
Jet Lag Prevention

Safe • Natural • Effective •
No Side Effects or Drug Interactions

NET 16 TABLETS:
SUFFICIENT FOR 30 HOURS OF FLYING